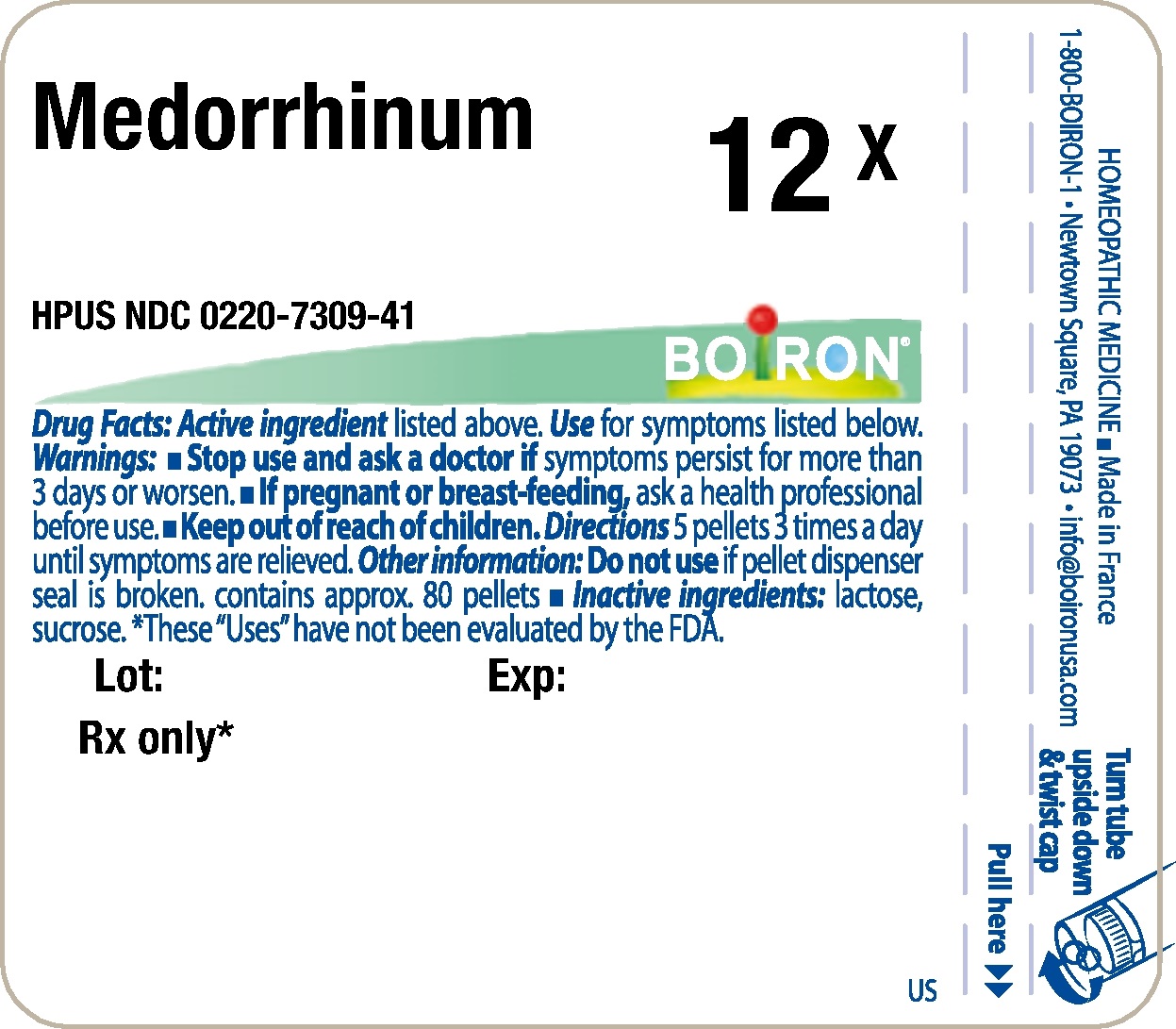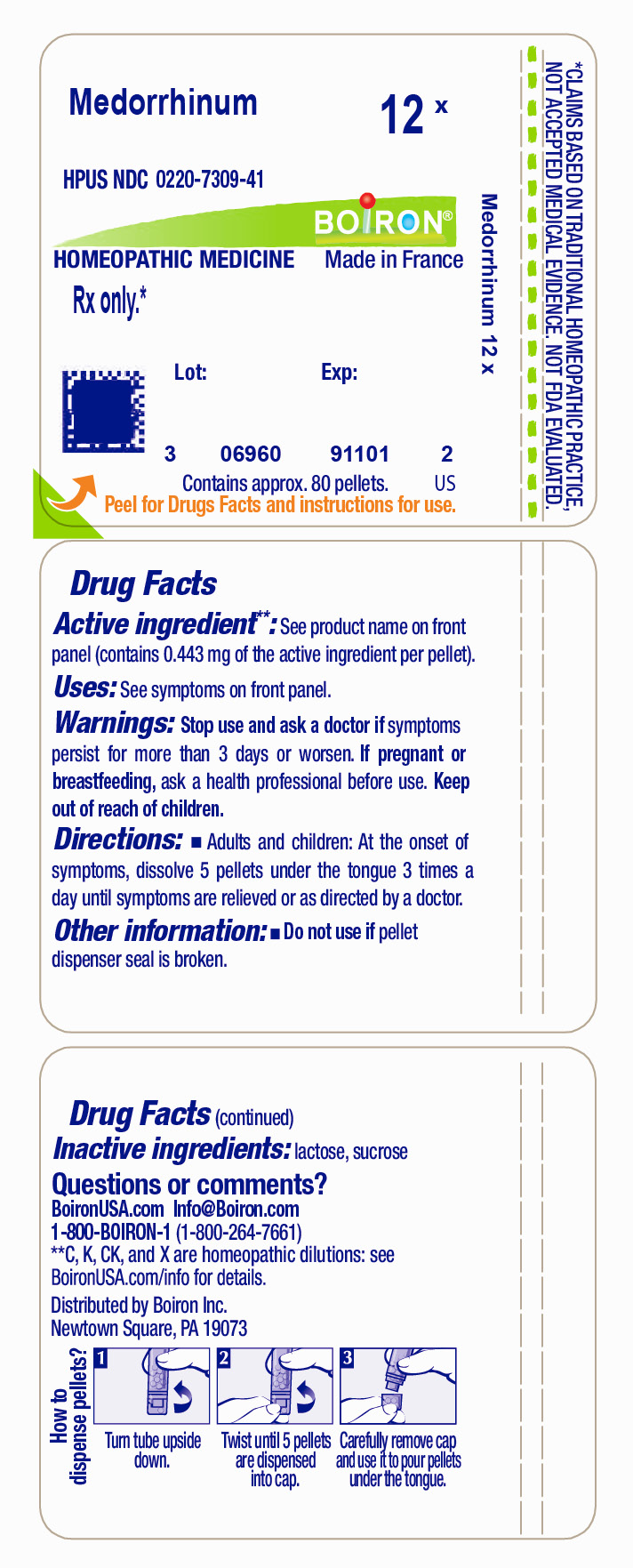 DRUG LABEL: Medorrhinum
NDC: 0220-7309 | Form: PELLET
Manufacturer: Laboratoires Boiron
Category: homeopathic | Type: HUMAN PRESCRIPTION DRUG LABEL
Date: 20231221

ACTIVE INGREDIENTS: GONORRHEAL URETHRAL SECRETION HUMAN 12 [hp_X]/1 1
INACTIVE INGREDIENTS: SUCROSE; LACTOSE

Medorrhinum 12X

Active Ingredients

Medorrhinum 12X

Use

Rx only*

Warnings

Stop use and ask a doctor if

symptoms persist for more than 3 days or worsen.

If pregnant or breast-feeding,

ask a health professional before use.

Directions

5 pellets 3 times a day until symptoms are relieved.

Other information

Do not use if pellet dispenser seal is broken.
contains approx. 80 pellets

Inactive ingredients

lactose, sucrose

Questions, Comments?

1-800-BOIRON-1
Newtown Square, PA 19073-3267
info@boironusa.com

*

These "Uses" have not been evaluated by the FDA.